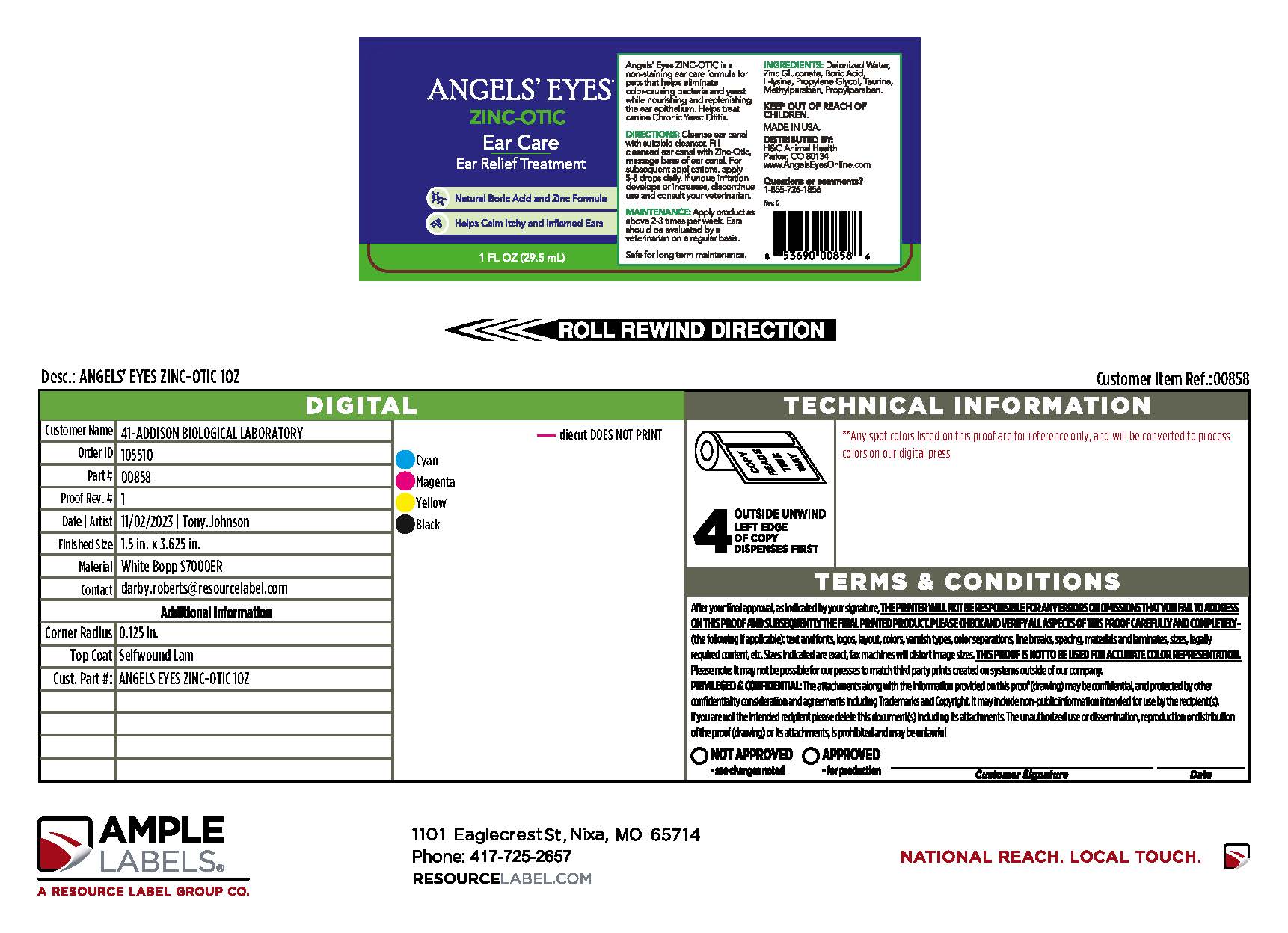 DRUG LABEL: ANGELS EYES
NDC: 86137-7509 | Form: SOLUTION
Manufacturer: H&C Animal Health
Category: animal | Type: OTC ANIMAL DRUG LABEL
Date: 20241217

ACTIVE INGREDIENTS: ZINC GLUCONATE .011 g/1 mL
INACTIVE INGREDIENTS: WATER; TAURINE; METHYLPARABEN; PROPYLPARABEN; LYSINE; BORIC ACID; PROPYLENE GLYCOL

ZINC OTIC

ANGELS' EYES®

ZINC-OTIC

Ear Care

Ear Relief Treatment

Natural Boric Acid and Zinc Formula

Helps Calm Itchy and Inflamed Ears

1 FL OZ (29.5 mL)

Angels' Eyes ZINC OTIC is a non-staining ear care formula for pets that helps eliminate odor-causing bacteria and yeast while nourishing and replenishing the ear epithelium. Helps treat canine Chronic Yeast Otitis.

DIRECTIONS:

Cleanse ear canal with suitable cleanser. Fill cleansed ear canal with Zinc-Otic, massage base of ear canal. For subsequent applications, apply 5-8 drops daily. If undue irritation develops or increases, discontinue use and consult your veterinarian.

MAINTENANCE:

Apply product as above 2-3 times per week. Ears should be evaluated by a veterinarian on a regular basis.

Safe for long term maintenance.

INGREDIENTS:

Deionized Water, Zinc Gluconate, Boric Acid, L-lysine, Propylene Glycol, Taurine, Methylparaben, Propylparaben.

KEEP OUT OF REACH OF CHILDREN.

MADE IN USA.

DISTRIBUTED BY:

H&C Animal Health

Parker, CO 80134

www.AngelEyesOnline.com

Questions or comments?

1-855-726-1856

Rev. 0

Package label, display panel

ANGELS' EYES®

ZINC-OTIC

Ear Care

Ear Relief Treatment

Natural Boric Acid and Zinc Formula

Helps Calm Itchy and Inflamed Ears

1 FL OZ (29.5 mL)

Angels' Eyes ZINC OTIC is a non-staining ear care formula for pets that helps eliminate odor-causing bacteria and yeast while nourishing and replenishing the ear epithelium. Helps treat canine Chronic Yeast Otitis.

DIRECTIONS:

Cleanse ear canal with suitable cleanser. Fill cleansed ear canal with Zinc-Otic, massage base of ear canal. For subsequent applications, apply 5-8 drops daily. If undue irritation develops or increases, discontinue use and consult your veterinarian.

MAINTENANCE:

Apply product as above 2-3 times per week. Ears should be evaluated by a veterinarian on a regular basis.

Safe for long term maintenance.

INGREDIENTS:

Deionized Water, Zinc Gluconate, Boric Acid, L-lysine, Propylene Glycol, Taurine, Methylparaben, Propylparaben.

KEEP OUT OF REACH OF CHILDREN.

MADE IN USA.

DISTRIBUTED BY:

H&C Animal Health

Parker, CO 80134

www.AngelEyesOnline.com

Questions or comments?

1-855-726-1856

Rev. 0